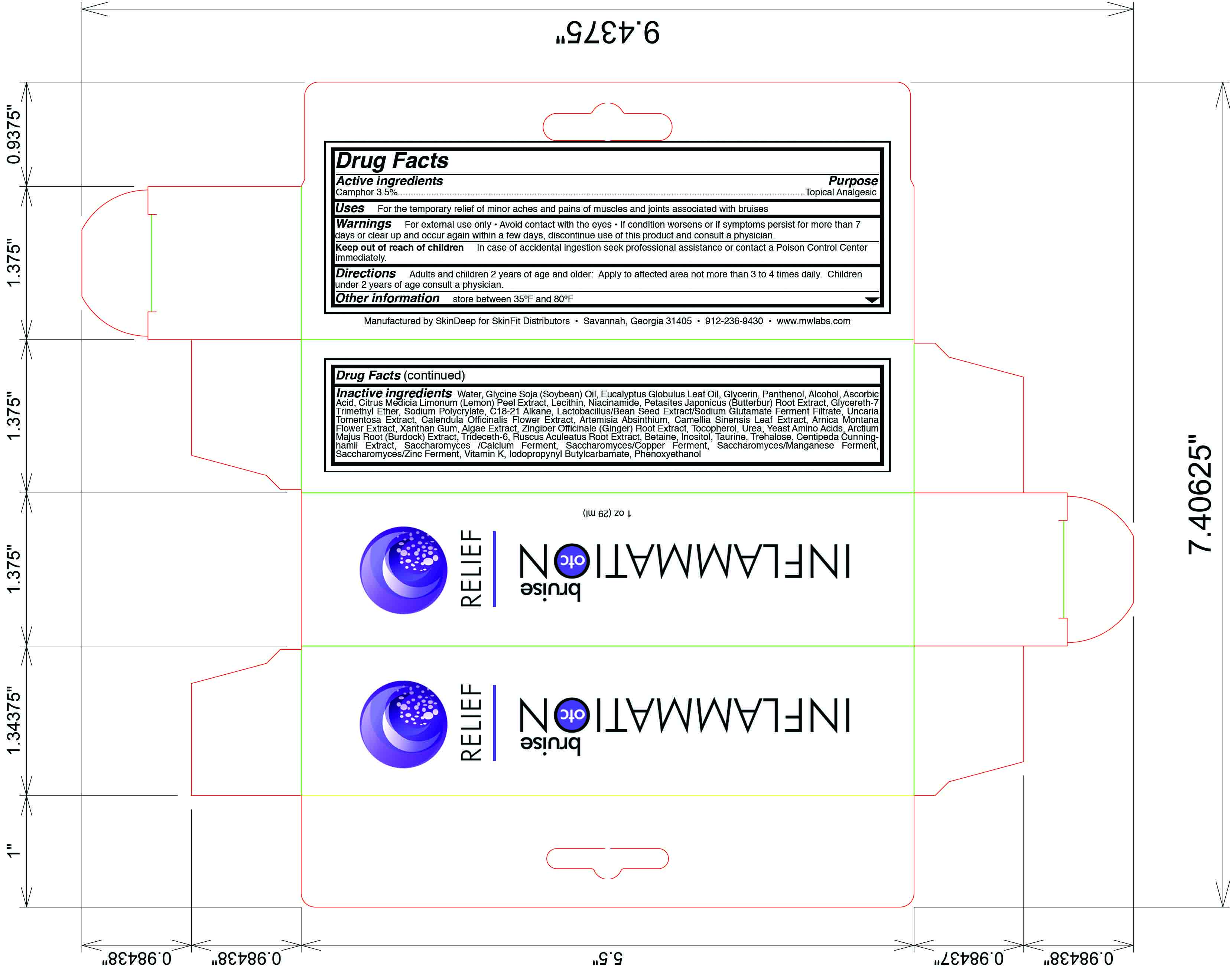 DRUG LABEL: Inflammation OTC
NDC: 45156-5502 | Form: LOTION
Manufacturer: Skin Deep
Category: otc | Type: HUMAN OTC DRUG LABEL
Date: 20110808

ACTIVE INGREDIENTS: Camphor (Natural) 32 g/1000 g
INACTIVE INGREDIENTS: Water; Glycerin; Alcohol; Dexpanthenol; Soybean Oil; Ascorbic Acid; Lemon Oil; Lecithin, Soybean; Niacinamide; Cat's Claw; Calendula Officinalis Flower; Wormwood; Green Tea Leaf; Arnica Montana Flower; Xanthan Gum; Carrageenan; Ginger; Alpha-Tocopherol; Urea; Saccharomyces Cerevisiae; Arctium Lappa Root; Trideceth-6; Ruscus Aculeatus Root; Betaine; Inositol; Taurine; Trehalose; Phytonadione; Iodopropynyl Butylcarbamate; Phenoxyethanol

Drug Facts

Active Ingredient

Camphor (3.16%)

Purpose

Counterirritant

Uses

For the temporary relief of minor aches and pains of muscles and joints associated with bruises

Warning

For external use only

Avoid contact with the eyes

If condition worsens or if symptoms persist for more than 7 days or clear up and occur again within a few days, discontinue use of this product and consult a physician

Do not apply to wounds or damaged skin

Do not bandage tightly

Keep out of reach of children

In case of accidental ingestion seek professional assistance or contact a poison control center immediately

Directions

Adults and children 2 years of age and older: Apply to affected area not more than 3 to 4 times daily

Children under 2 years of age: Consult a physician

Inactive Ingredients

water, glycine soja (soybean) oil, glycerin, panthenol, alcohol, ascorbic acid, citrus medica limonum (lemon) peel extract, niacinamide, petasites japonicus (butterbur) root extract, glycereth-7 trimethyl ether, sodium polycrylate, c18-21 alkane, lactobacillus/bean seed extract/sodium glutamate ferment filtrate, uncaria tomentosa extract, calendula officinale (ginger) root extract, tocopherol, urea, yeast amino acid, arctium majus root (burdock) extract, trideceth-6, ruscus aculeatus root extract, inositol, taurine, trehalose, centipeda cunninghamii extract, saccharomyces/calcium ferment, saccharomyces/copper ferment, saccharomyces/manganese ferment, saccaromyces/zinc ferment, vitamin k, iodopropynyl butylcarbamate, phenoxyethanol

Questions and Comments

Store between 35 F and 80 F

call 1-912-236-9430 weekdays

Principal Display Panel

Inflammation OTC

Bruise Relief

Net wt 1 oz. (28.5 mL)

Manufacture by SkinDeep for SkinFit Distributors

Savannah, Georgia 31405

Tel: 912-236-9430

www.mwlabs.com